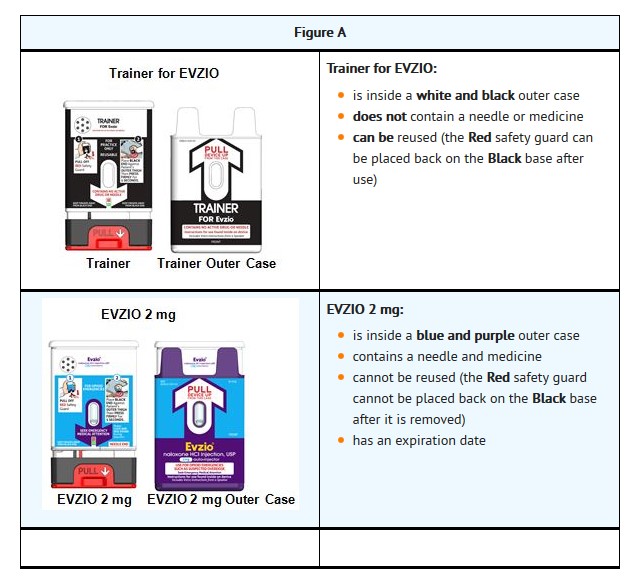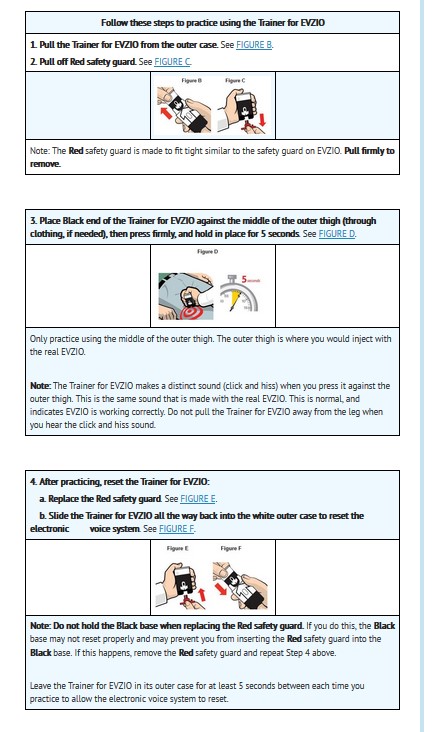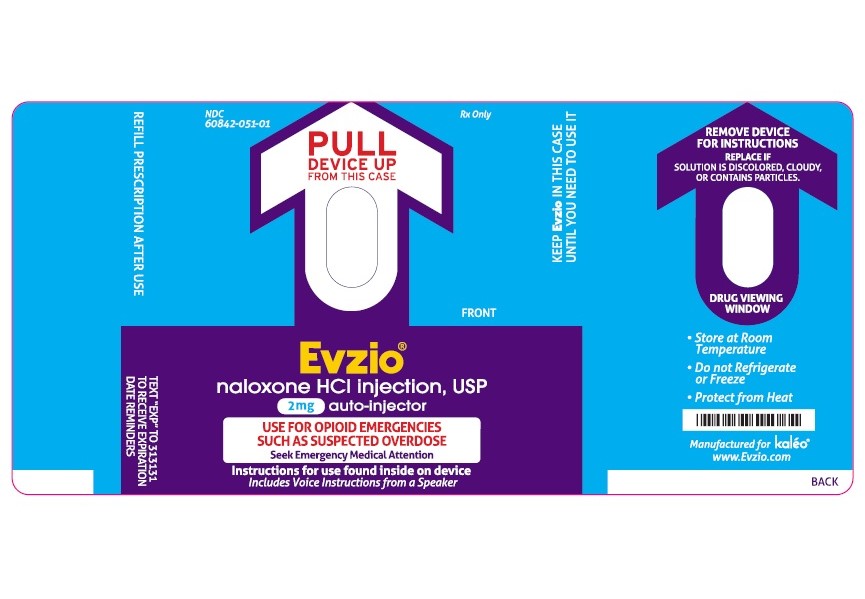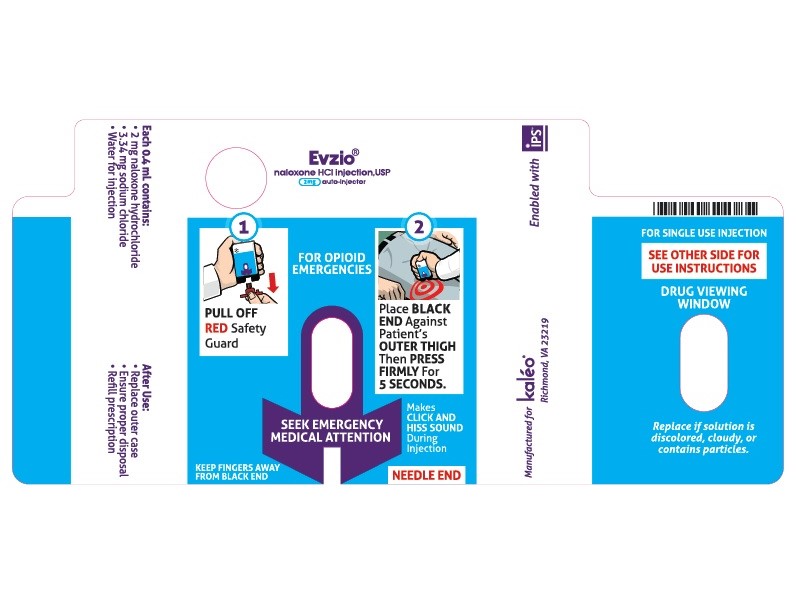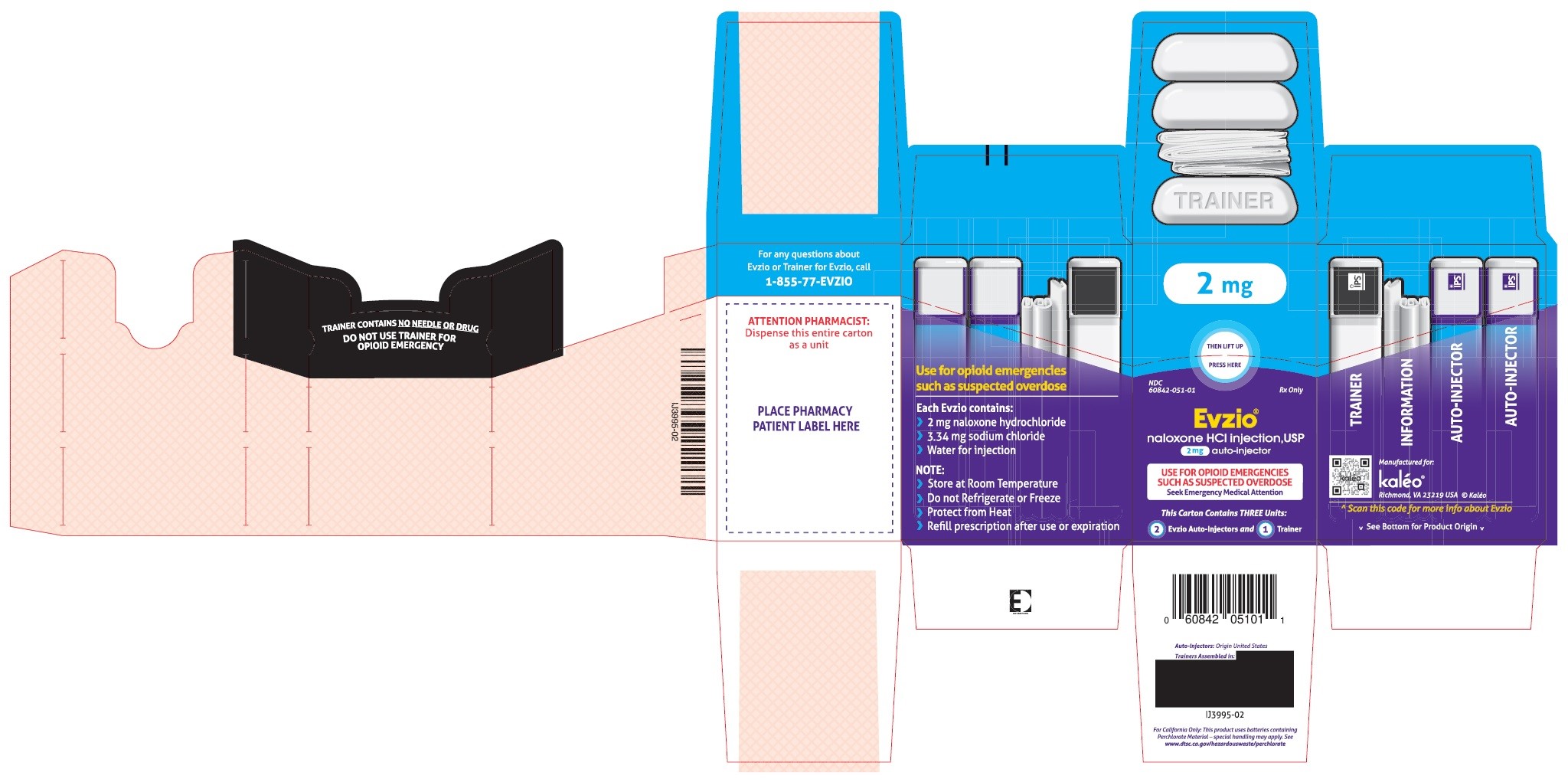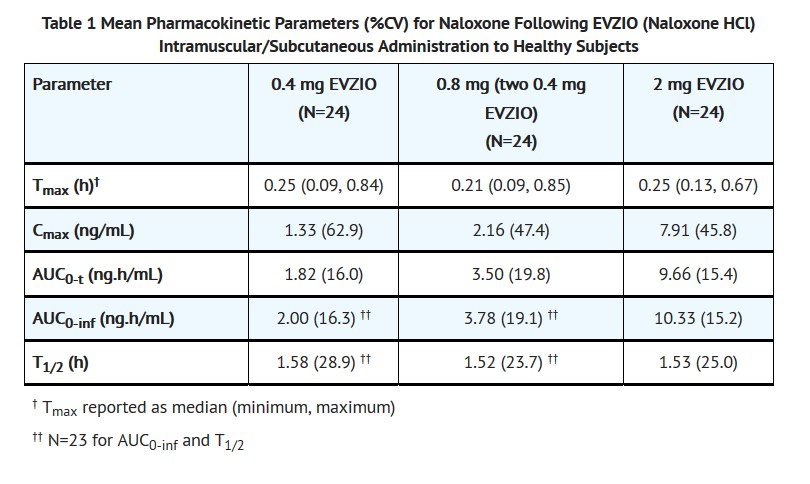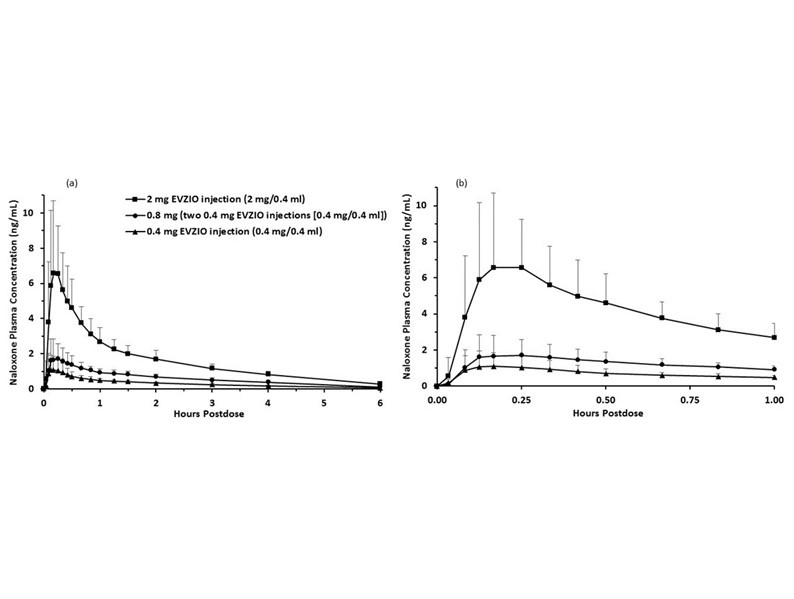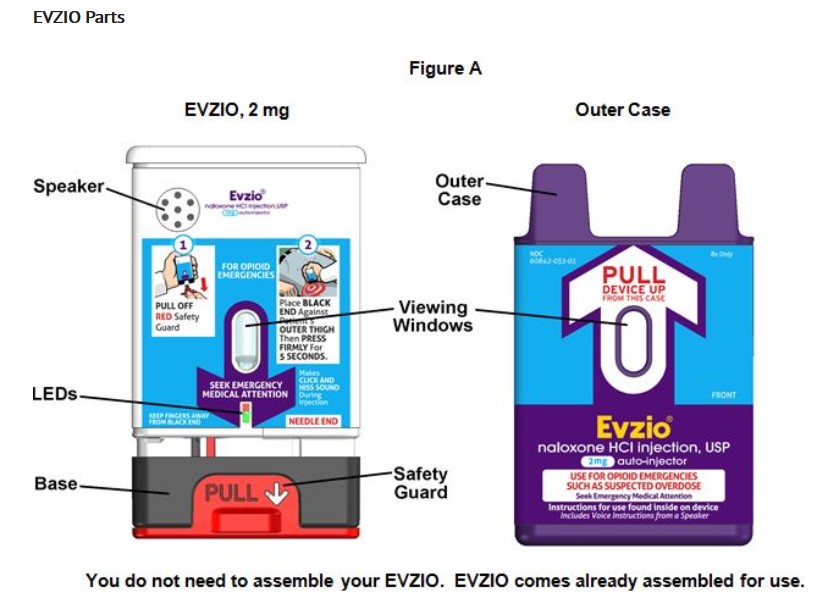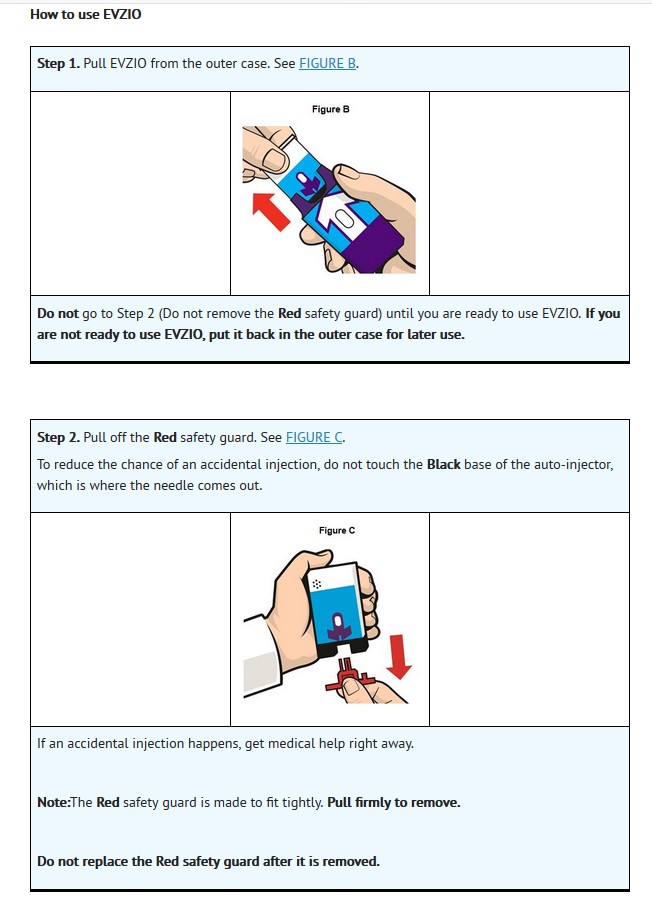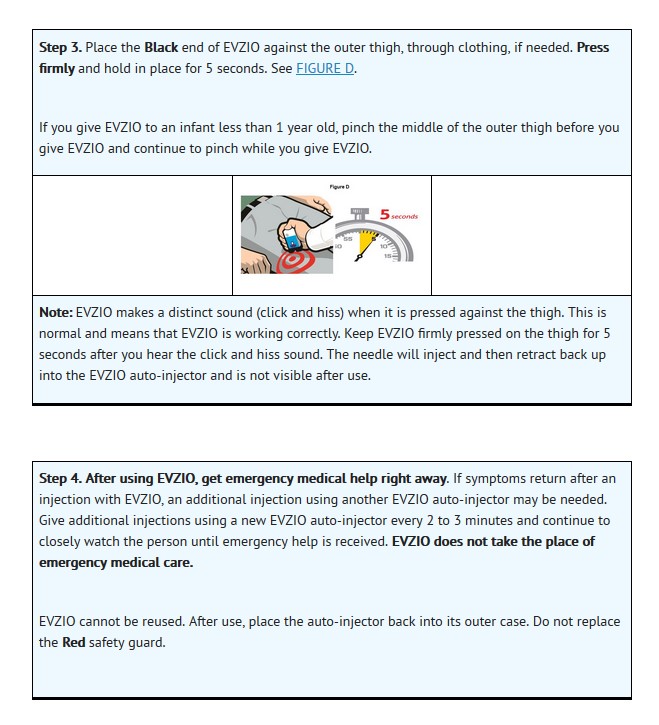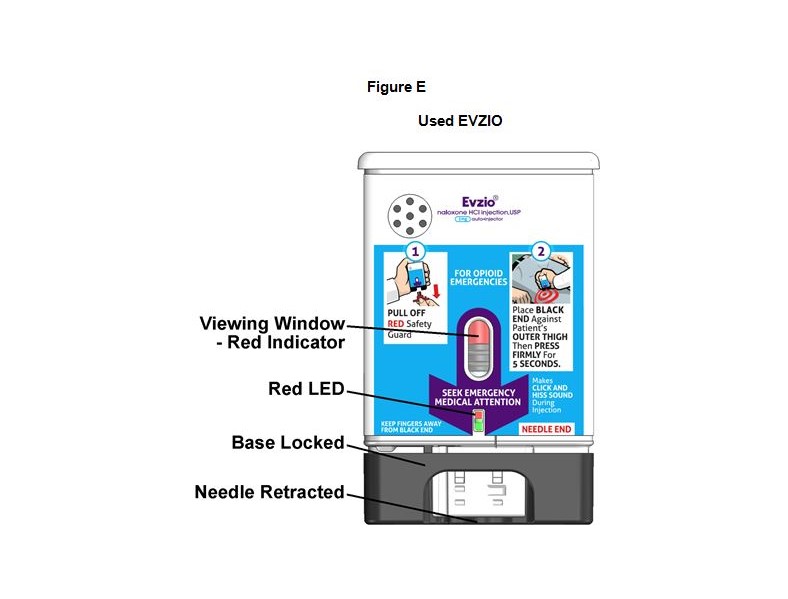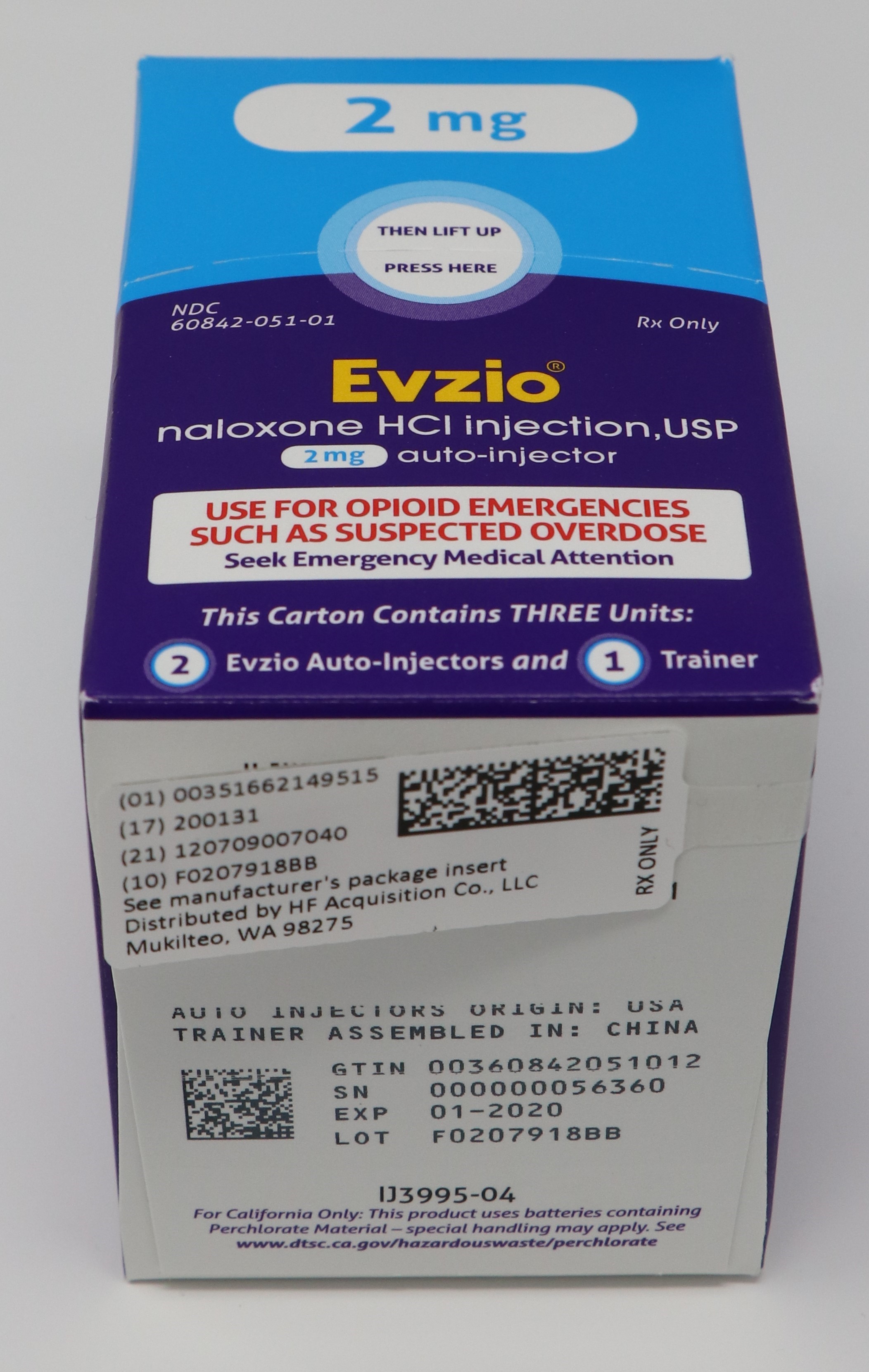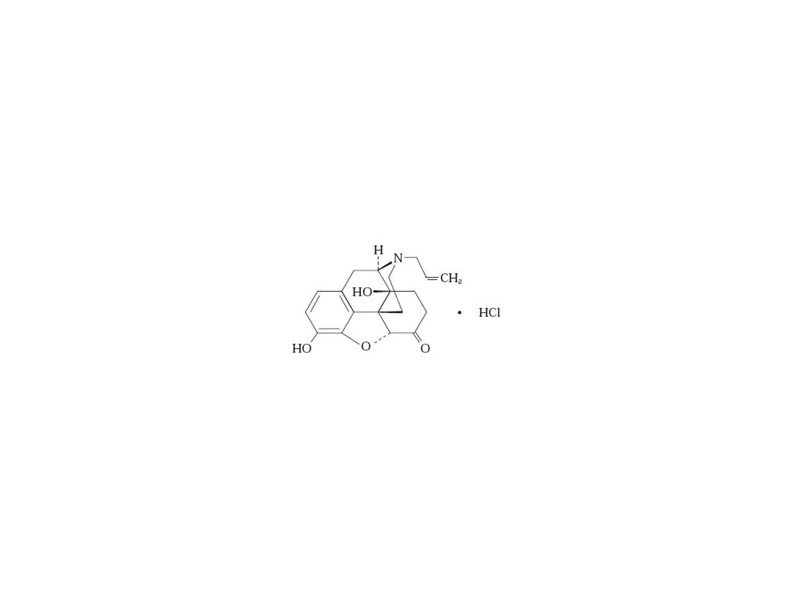 DRUG LABEL: EVZIO(R) NALOXONE HCl
NDC: 51662-1495 | Form: INJECTION, SOLUTION
Manufacturer: HF Acquisition Co LLC, DBA HealthFirst
Category: prescription | Type: HUMAN PRESCRIPTION DRUG LABEL
Date: 20200223

ACTIVE INGREDIENTS: NALOXONE HYDROCHLORIDE 2 mg/0.4 mL
INACTIVE INGREDIENTS: WATER; SODIUM CHLORIDE 3.34 mg/0.4 mL; HYDROCHLORIC ACID

EVZIO(R) NALOXONE HCl INJECTION, USP 2mg AUTO-INJECTOR 2 PACK

HIGHLIGHTS OF PRESCRIBING INFORMATION

These highlights do not include all the information needed to use EVZIO® safely and effectively. See full prescribing information for EVZIO.
EVZIO® (naloxone hydrochloride injection) Auto-Injector for intramuscular or subcutaneous use
2 mg
Initial U.S. Approval: 1971

INDICATIONS AND USAGE

EVZIO is an opioid antagonist indicated for the emergency treatment of known or suspected opioid overdose, as manifested by respiratory and/or central nervous system depression in adults and pediatric patients. (1)

EVZIO is intended for immediate administration as emergency therapy in settings where opioids may be present. (1)

EVZIO is not a substitute for emergency medical care. (1)

DOSAGE AND ADMINISTRATION

EVZIO is for intramuscular or subcutaneous use only. (2-2.1)
Seek emergency medical care immediately after use. (2-2.1)
Administer EVZIO to adult or pediatric patients into the anterolateral aspect of the thigh, through clothing if necessary. (2-2.2)
Administer additional doses of EVZIO, using a new auto-injector, if the patient does not respond or responds and then relapses into respiratory depression. Additional doses of EVZIO may be given every 2 to 3 minutes until emergency medical assistance arrives. (2-2.2)
Additional supportive and/or resuscitative measures may be helpful while awaiting emergency medical assistance. (2-2.2)
In pediatric patients under the age of one, the caregiver should pinch the thigh muscle while administering the dose. (2-2.2)
If the electronic voice instruction system does not operate properly, EVZIO will still deliver the intended dose of naloxone hydrochloride when used according to the printed instructions on the flat surface of its label. (2-2.1)

DOSAGE FORMS AND STRENGTHS

Injection: 2 mg/0.4 mL naloxone hydrochloride solution in a pre-filled auto-injector. (3

CONTRAINDICATIONS

Hypersensitivity to naloxone hydrochloride. (4)

WARNINGS AND PRECAUTIONS

Risk of Recurrent Respiratory and CNS Depression: Due to the duration of action of naloxone relative to the opioid, keep the patient under continued surveillance and administer repeated doses of naloxone using a new EVZIO, as necessary, while awaiting emergency medical assistance. (5-5.1)
Risk of Limited Efficacy with Partial Agonists or Mixed Agonists/Antagonists: Reversal of respiratory depression caused by partial agonists or mixed agonists/antagonists such as buprenorphine and pentazocine, may be incomplete. Larger or repeat doses may be required. (5-5.2)
Precipitation of Severe Opioid Withdrawal: Use in patients who are opioid dependent may precipitate opioid withdrawal. In neonates, opioid withdrawal may be life-threatening if not recognized and properly treated. Monitor for the development of opioid withdrawal. (5-5.3)
Risk of Cardiovascular (CV) Effects: Abrupt postoperative reversal of opioid depression may results in adverse CV effects. These events have primarily occurred in patients who had pre-existing CV disorders or received other drugs that may have similar CV effects. Monitor these patients closely in an appropriate healthcare setting after use of naloxone hydrochloride. (5-5.3)

ADVERSE REACTIONS

The following adverse reactions were most commonly observed in EVZIO clinical studies: dizziness and injection site erythema. (6)

To report SUSPECTED ADVERSE REACTIONS, contact contact kaleo, Inc. at 1-855-773-8946 or FDA at 1-800-FDA-1088 or www.fda.gov/medwatch.

See 17 for PATIENT COUNSELING INFORMATION and FDA-approved patient labeling.

Revised: 10/2016

1 INDICATIONS & USAGE

EVZIO is an opioid antagonist indicated for the emergency treatment of known or suspected opioid overdose, as manifested by respiratory and/or central nervous system depression in adults and pediatric patients.

EVZIO is intended for immediate administration as emergency therapy in settings where opioids may be present.

EVZIO is not a substitute for emergency medical care.

2 DOSAGE & ADMINISTRATION

2.1 Important Administration Instructions

EVZIO is for intramuscular and subcutaneous use only.

Because treatment of suspected opioid overdose must be performed by someone other than the patient, instruct the prescription recipient to inform those around them about the presence of EVZIO and the Instructions for Use.

Instruct the patient or caregiver to read the Instructions for Use at the time they receive a prescription for EVZIO. Emphasize the following instructions to the patient or caregiver:

Seek emergency medical care immediately after use. Since the duration of action of most opioids exceeds that of naloxone hydrochloride and the suspected opioid overdose may occur outside of supervised medical settings, seek immediate emergency medical assistance, keep the patient under continued surveillance until emergency personnel arrive, and administer repeated doses of EVZIO as necessary. Always seek emergency medical assistance in the event of a suspected potentially life-threatening opioid emergency after administration of the first dose of EVZIO.
Additional doses of EVZIO may be required until emergency medical assistance becomes available.
Do not attempt to reuse EVZIO. Each EVZIO contains a single dose of naloxone.
Visually inspect EVZIO through the viewing window for particulate matter and discoloration prior to administration. Do not administer unless the solution is clear and the glass container is undamaged.
EVZIO must be administered according to the printed instructions on the device label or the electronic voice instructions (EVZIO contains a speaker that provides voice instructions to guide the user through each step of the injection). If the EVZIO electronic voice instruction system does not operate properly, EVZIO will still deliver the intended dose of naloxone hydrochloride when used according to the printed instructions on its label.
Once the red safety guard is removed, EVZIO must be used immediately or disposed of properly. Do not attempt to replace the red safety guard once it is removed.

Upon actuation, EVZIO automatically inserts the needle intramuscularly or subcutaneously, delivers the naloxone hydrochloride injection, and retracts the needle fully into its housing. Post injection, the black base locks in place, a red indicator appears in the viewing window, and electronic visual and audible instructions signal that EVZIO has delivered the intended dose of naloxone hydrochloride and instructs the user to seek emergency medical attention.

2.2 Dosing Information

Initial Dosing

Administer the initial dose of EVZIO to adult or pediatric patients intramuscularly or subcutaneously into the anterolateral aspect of the thigh, through clothing if necessary, and seek emergency medical assistance. Administer EVZIO as quickly as possible because prolonged respiratory depression may result in damage to the central nervous system or death.

Repeat Dosing

The requirement for repeat doses of EVZIO depends upon the amount, type, and route of administration of the opioid being antagonized.

If the desired response is not obtained after 2 or 3 minutes, an additional dose of EVZIO may be administered. If there is still no response and additional doses are available, additional doses of EVZIO may be administered every 2 to 3 minutes until emergency medical assistance arrives. Additional supportive and/or resuscitative measures may be helpful while awaiting emergency medical assistance.

If the patient responds to EVZIO and relapses back into respiratory depression before emergency assistance arrives, an additional dose of EVZIO may be administered.

Reversal of respiratory depression by partial agonists or mixed agonist/antagonists, such as buprenorphine and pentazocine, may be incomplete and may require higher doses of naloxone hydrochloride or repeated administration of EVZIO.

Dosing in Adults and Pediatric Patients over Age One Year

Instruct patients or their caregivers to administer EVZIO according to the Instructions for Use, intramuscularly or subcutaneously.

Dosing in Pediatric Patients under Age One Year

In pediatric patients under the age of one year, the caregiver should pinch the thigh muscle while administering EVZIO. Carefully observe the administration site for signs of infection following injection and resolution of the opioid emergency.

There may be clinical settings, particularly the postpartum period in neonates with known or suspected exposure to maternal opioid use, where it is preferable to avoid the abrupt precipitation of opioid withdrawal symptoms. In these settings, consider use of an alternative, naloxone product which can be titrated to effect and, where applicable, dosed according to weight [see Use in Specific Populations (8.4)].

3 DOSAGE FORMS & STRENGTHS

2 mg Injection: 2 mg/0.4 mL naloxone hydrochloride solution in a pre-filled auto-injector. Each EVZIO 2 mg delivers 2 mg naloxone hydrochloride injection (0.4 mL).

4 CONTRAINDICATIONS

EVZIO is contraindicated in patients known to be hypersensitive to naloxone hydrochloride or to any of the other ingredients.

5 WARNINGS AND PRECAUTIONS

5.1 Risk of Recurrent Respiratory and Central Nervous System Depression

The duration of action of most opioids may exceed that of EVZIO resulting in a return of respiratory and/or central nervous system depression after an initial improvement in symptoms. Therefore, it is necessary to seek emergency medical assistance immediately after delivering the first dose of EVZIO. Keep the patient under continued surveillance, and administer additional doses of EVZIO as necessary [see Dosage and Administration (2.2)]. Additional supportive and/or resuscitative measures may be helpful while awaiting emergency medical assistance.

5.2 Risk of Limited Efficacy with Partial Agonists or Mixed Agonist/Antagonists

Reversal of respiratory depression by partial agonists or mixed agonist/antagonists such as buprenorphine and pentazocine, may be incomplete. Larger or repeat doses of naloxone hydrochloride may be required to antagonize buprenorphine because the latter has a long duration of action due to its slow rate of binding and subsequent slow dissociation from the opioid receptor [see Dosage and Administration (2.3)]. Buprenorphine antagonism is characterized by a gradual onset of the reversal effects and a decreased duration of action of the normally prolonged respiratory depression.

5.3 Precipitation of Severe Opioid Withdrawal

The use of EVZIO in patients who are opioid dependent may precipitate an acute abstinence syndrome characterized by the following signs and symptoms: body aches, diarrhea, tachycardia, fever, runny nose, sneezing, piloerection, sweating, yawning, nausea or vomiting, nervousness, restlessness or irritability, shivering or trembling, abdominal cramps, weakness, and increased blood pressure. In neonates, opioid withdrawal may be life-threatening if not recognized and properly treated and may include the following signs and symptoms: convulsions, excessive crying and hyperactive reflexes. Monitor patients for the development of the signs and symptoms of opioid withdrawal.

Abrupt postoperative reversal of opioid depression after using naloxone hydrochloride may result in nausea, vomiting, sweating, tremulousness, tachycardia, hypotension, hypertension, seizures, ventricular tachycardia and fibrillation, pulmonary edema, and cardiac arrest. Death, coma, and encephalopathy have been reported as sequelae of these events. These events have primarily occurred in patients who had pre-existing cardiovascular disorders or received other drugs that may have similar adverse cardiovascular effects. Although a direct cause and effect relationship has not been established, after use of naloxone hydrochloride, monitor patients with pre-existing cardiac disease or patients who have received medications with potential adverse cardiovascular effects for hypotension, ventricular tachycardia or fibrillation, and pulmonary edema in an appropriate healthcare setting. It has been suggested that the pathogenesis of pulmonary edema associated with the use of naloxone hydrochloride is similar to neurogenic pulmonary edema, i.e., a centrally mediated massive catecholamine response leading to a dramatic shift of blood volume into the pulmonary vascular bed resulting in increased hydrostatic pressures.

6 ADVERSE REACTIONS

The following serious adverse reactions are discussed elsewhere in the labeling:

Precipitation of Severe Opioid Withdrawal [see Warnings and Precautions (5.3)]

Because clinical studies are conducted under widely varying conditions, adverse reaction rates observed in the clinical studies of a drug cannot be directly compared to the rates in the clinical studies of another drug and may not reflect the rates observed in practice.

The following adverse reactions were observed in EVZIO clinical studies. In two pharmacokinetic studies with a total of 54 healthy adult subjects exposed to 0.4 mg EVZIO, 0.8 mg EVZIO (two 0.4 mg EVZIOs) or 2 mg EVZIO, adverse reactions occurring in more than one subject were dizziness and injection site erythema.

The following adverse reactions have been identified during post-approval use of naloxone hydrochloride in the post-operative setting. Because these reactions are reported voluntarily from a population of uncertain size, it is not always possible to reliably estimate their frequency or establish a causal relationship to drug exposure: Hypotension, hypertension, ventricular tachycardia and fibrillation, dyspnea, pulmonary edema, and cardiac arrest. Death, coma, and encephalopathy have been reported as sequelae of these events. Excessive doses of naloxone hydrochloride in post-operative patients have resulted in significant reversal of analgesia and have caused agitation [see Warnings and Precautions (5.3)].

Other events that have been reported in post-marketing use of EVZIO include agitation, disorientation, confusion, and anger.

Abrupt reversal of opioid effects in persons who were physically dependent on opioids has precipitated an acute withdrawal syndrome. Signs and symptoms have included: body aches, fever, sweating, runny nose, sneezing, piloerection, yawning, weakness, shivering or trembling, nervousness, restlessness or irritability, diarrhea, nausea or vomiting, abdominal cramps, increased blood pressure, tachycardia. In the neonate, opioid withdrawal signs and symptoms also included: convulsions, excessive crying, hyperactive reflexes [see Warnings and Precautions (5.3)].

8 USE IN SPECIFIC POPULATIONS

8.1 Pregnancy

Risk Summary

The limited available data on naloxone use in pregnant women are not sufficient to inform a drug-associated risk. However, there are risks to the fetus of the opioid-dependent mother with use of naloxone [see Clinical Considerations]. In animal reproduction studies, no embryotoxic or teratogenic effects were observed in mice and rats treated with naloxone hydrochloride during the period of organogenesis at doses equivalent to 4-times and 8-times, respectively, the dose of a 50 kg human given 10 mg [see Data].

The estimated background risk of major birth defects and miscarriage for the indicated population is unknown. All pregnancies have a background risk of birth defect, loss, or other adverse outcomes. In the U.S. general population, the estimated background risk of major birth defects and miscarriage in clinically recognized pregnancies is 2% to 4% and 15% to 20%, respectively.

Clinical Considerations

Fetal/Neonatal adverse reactions

Naloxone hydrochloride crosses the placenta, and may precipitate withdrawal in the fetus as well as in the opioid-dependent mother [see Warnings and Precautions (5.3)]. The fetus should be evaluated for signs of distress after EVZIO is used. Careful monitoring is needed until the fetus and mother are stabilized.

Data

Animal Data

Naloxone hydrochloride was administered during organogenesis to mice and rats at doses 4-times and 8-times, respectively, the dose of 10 mg/day given to a 50 kg human (when based on body surface area or mg/m2). These studies demonstrated no embryotoxic or teratogenic effects due to naloxone hydrochloride.

8.2 Lactation

Risk Summary

There is no information regarding the presence of naloxone in human milk, or the effects of naloxone on the breastfed infant or on milk production. Studies in nursing mothers have shown that naloxone does not affect prolactin or oxytocin hormone levels. Naloxone is minimally orally bioavailable. The developmental and health benefits of breastfeeding should be considered along with the mother’s clinical need for EVZIO and any potential adverse effects on the breastfed infant from EVZIO or from the underlying maternal condition.

8.4 Pediatric Use

The safety and effectiveness of EVZIO (for intramuscular and subcutaneous use) have been established in pediatric patients of all ages for the emergency treatment of known or suspected opioid overdose. Use of naloxone hydrochloride in all pediatric patients is supported by adult bioequivalence studies coupled with evidence from the safe and effective use of another naloxone hydrochloride injectable product. No pediatric studies were conducted for EVZIO.

Absorption of naloxone hydrochloride following subcutaneous or intramuscular administration in pediatric patients may be erratic or delayed. Even when the opiate-intoxicated pediatric patient responds appropriately to naloxone hydrochloride injection, he/she must be carefully monitored for at least 24 hours as a relapse may occur as naloxone is metabolized.

In opioid-dependent pediatric patients, (including neonates), administration of naloxone hydrochloride may result in an abrupt and complete reversal of opioid effects, precipitating an acute opioid withdrawal syndrome. There may be clinical settings, particularly the postpartum period in neonates with known or suspected exposure to maternal opioid use, where it is preferable to avoid the abrupt precipitation of opioid withdrawal symptoms. Unlike acute opioid withdrawal in adults, acute opioid withdrawal in neonates manifesting as seizures may be life-threatening if not recognized and properly treated. Other signs and symptoms in neonates may include excessive crying and hyperactive reflexes. In these settings where it may be preferable to avoid the abrupt precipitation of acute opioid withdrawal symptoms, consider use of an alternative, naloxone hydrochloride product that can be dosed according to weight and titrated to effect. [see Warnings and Precautions (5-5.3)].

In pediatric patients under the age of one year, the caregiver should pinch the thigh muscle while administering EVZIO. Carefully observe the administration site for evidence of residual needle parts, signs of infection, or both. [see Dosing Information (2-2.2)].

8.5 Geriatric Use

Geriatric patients have a greater frequency of decreased hepatic, renal, or cardiac function and of concomitant disease or other drug therapy. Therefore, the systemic exposure of naloxone can be higher in these patients.

Clinical studies of naloxone hydrochloride did not include sufficient numbers of subjects aged 65 and over to determine whether they respond differently from younger subjects. Other reported clinical experience has not identified differences in responses between the elderly and younger patients.

11 DESCRIPTION

EVZIO (naloxone hydrochloride injection, USP) is a pre-filled, single-use auto-injector. EVZIO is not made with natural rubber latex. Chemically, naloxone hydrochloride is the hydrochloride salt of 17-Allyl-4,5α-epoxy-3,14-dihydroxymorphinan-6-one hydrochloride with the following structure:

C19H21NO4• HCl

M.W. 363.84

Naloxone hydrochloride occurs as a white to slightly off-white powder, and is soluble in water, in dilute acids, and in strong alkali; slightly soluble in alcohol; practically insoluble in ether and in chloroform.

Each 0.4 mL of EVZIO contains 2 mg naloxone hydrochloride, 3.34 mg of sodium chloride, hydrochloric acid to adjust pH, and water for injection. The pH range is 3.0 to 4.5.

12 CLINICAL PHARMACOLOGY

12.1 Mechanism of Action

Naloxone hydrochloride is an opioid antagonist that antagonizes opioid effects by competing for the same receptor sites.

Naloxone hydrochloride reverses the effects of opioids, including respiratory depression, sedation, and hypotension. Also, it can reverse the psychotomimetic and dysphoric effects of agonist-antagonists such as pentazocine.

12.2 Pharmacodynamics

When naloxone hydrochloride is administered intravenously, the onset of action is generally apparent within two minutes. The time to onset of action is shorter for intravenous compared to subcutaneous or intramuscular routes of administration.

The duration of action is dependent upon the dose and route of administration of naloxone hydrochloride.

12.3 Pharmacokinetics

In a pharmacokinetic study in 30 healthy subjects, a single 0.4 mg subcutaneous or intramuscular naloxone injection administered using EVZIO provides equivalent naloxone AUC and 15% greater naloxone Cmax in comparison to a single 0.4 mg subcutaneous or intramuscular naloxone injection administered using a standard syringe.

Following a single 0.4 mg EVZIO injection, the median Tmax of naloxone was reached at 0.25 hours (range 0.08 to 1.23 hours), with a mean Cmax value of 1.24 (51.4% CV) ng/mL. The mean plasma half-life of naloxone in healthy adults was 1.28 (38.0% CV) hours. In the same study, following administration of a single dose of 0.4 mg naloxone injection using a standard syringe, the median Tmax was 0.33 hours (range 0.08 to 2.03 hours) and the mean Cmax value was 1.07 (45.1% CV) ng/mL. The mean plasma half-life was 1.36 (23.5% CV) hours.

A second pharmacokinetic study in 24 healthy subjects using a crossover design, evaluated a single 0.4 mg EVZIO injection, a single 2 mg EVZIO injection, and two 0.4 mg EVZIO injections administered two minutes apart (0.8 mg naloxone hydrochloride total). The pharmacokinetic parameters obtained in this study are shown in Table 1 and the plasma concentration time profiles of naloxone are in Figure 1.

Figure 1 Mean ± SD Plasma Concentration of Naloxone, (a) 0-6 h and (b) 0-1h Following Intramuscular/Subcutaneous Administration using EVZIO

Distribution
Following parenteral administration, naloxone is distributed in the body and readily crosses the placenta. Plasma protein binding occurs but is relatively weak. Plasma albumin is the major binding constituent but significant binding of naloxone also occurs to plasma constituents other than albumin. It is not known whether naloxone is excreted into human milk.

Elimination
Following a single 0.4 mg EVZIO injection, the mean plasma half-life of naloxone in healthy adults was 1.58 (28.9% CV) hours and 1.53 (25% CV) hours following a single 2 mg EVZIO injection. In a neonatal study of naloxone injection, the mean (± SD) plasma half-life was observed to be 3.1 (± 0.5) hours.

Metabolism
Naloxone hydrochloride is metabolized in the liver, primarily by glucuronide conjugation with naloxone-3-glucoronide as the major metabolite.

Excretion
After an oral or intravenous dose, about 25-40% of naloxone is excreted as metabolites in urine within 6 hours, about 50% in 24 hours, and 60-70% in 72 hours.

13 NONCLINICAL TOXICOLOGY

13.1 Carcinogenesis, Mutagenesis, Impairment of Fertility

Carcinogenesis

Long-term animal studies to evaluate the carcinogenic potential of naloxone have not been completed.

Mutagenesis

Naloxone was weakly positive in the Ames mutagenicity and in the in vitro human lymphocyte chromosome aberration test but was negative in the in vitro Chinese hamster V79 cell HGPRT mutagenicity assay and in the in vivo rat bone marrow chromosome aberration study.

Impairment of Fertility

Reproduction studies conducted in mice and rats at doses 4-times and 8-times, respectively, the dose of a 50 kg human given 10 mg/day (when based on surface area or mg/m2), demonstrated no adverse effect of naloxone hydrochloride on fertility.

16 HOW SUPPLIED/STORAGE AND HANDLING

EVZIO(R) NALOXONE HCl INJECTION, USP is supplied in the following dosage forms.
NDC 51662-1495-1
EVZIO(R) NALOXONE HCl INJECTION, USP 2mg AUTO-INJECTOR 2 PACK

HF Acquisition Co LLC, DBA HealthFirst
Mukilteo, WA 98275

Also supplied in the following manufacture supplied dosage forms

16.1 How Supplied

Carton containing two EVZIO (naloxone hydrochloride injection, USP) 2 mg auto-injectors and a single Trainer for EVZIO - NDC 60842-051-01

16.2 Storage and Handling

Store EVZIO in the outer case provided.

Store at controlled room temperature 15°C to 25°C (59°F to 77°F) excursions permitted between 4°C and 40°C (between 39°F and 104°F).

Before using, check to make sure the solution in the auto-injector is not discolored. Replace EVZIO if the solution is discolored or contains a precipitate.

17 PATIENT COUNSELING INFORMATION

Advise the patient and family members or caregivers to read the FDA-approved patient labeling (Patient Information and Instructions for Use).

Instruct patients and their family members or caregivers to:

Become familiar with the following information contained in the carton as soon as they receive EVZIO:

EVZIO Instructions for Use
Trainer for EVZIO Instructions for Use
Trainer for EVZIO

Become familiar with the device labeling color scheme of EVZIO and the Trainer for EVZIO

The 2 mg dosage form of EVZIO is blue and purple.
The Trainer for EVZIO is black and white.

Practice using the Trainer before EVZIO is needed.

Each EVZIO can only be used one time; however, Trainer for EVZIO can be re-used for training purposes and its red safety guard can be removed and replaced.
Both EVZIO and Trainer for EVZIO incorporate the electronic voice instruction system.

It is recommended that patients and caregivers become familiar with the Trainer for EVZIO provided and read the Instructions for Use; however, untrained caregivers or family members should still attempt to use EVZIO during a suspected opioid overdose while awaiting definitive emergency medical care.

Recognition of Opioid Overdose

Instruct the patients and their family members or caregivers how to recognize the signs and symptoms of an opioid overdose requiring the use of EVZIO such as the following:

Extreme sleepiness - inability to awaken a patient verbally or upon a firm sternal rub.
Breathing problems - this can range from slow or shallow breathing to no breathing in a patient who cannot be awakened.
Other signs and symptoms that may accompany sleepiness and breathing problems include the following:

Extremely small pupils (the black circle in the center of the colored part of the eye) sometimes called “pinpoint pupils.”
Slow heartbeat and/or low blood pressure.

Risk of Recurrent Respiratory and Central Nervous System Depression

Instruct patients and their family members or caregivers that since the duration of action of most opioids may exceed that of EVZIO, they must seek immediate emergency medical assistance after the first dose of EVZIO and keep the patient under continued surveillance [see Dosage and Administration (2.2), Warnings and Precautions (5-5.3)].

Limited Efficacy for/with Partial Agonists or Mixed Agonist/Antagonists

Instruct patients and their family members or caregivers that the reversal of respiratory depression caused by partial agonists or mixed agonist/antagonists such as buprenorphine and pentazocine, may be incomplete and may require higher doses of naloxone hydrochloride or repeated administration of EVZIO [see Dosage and Administration (2-2.2), Warnings and Precautions (5-5.3)].

Precipitation of Severe Opioid Withdrawal

Instruct patients and their family members or caregivers that the use of EVZIO in patients who are opioid dependent may precipitate an acute abstinence syndrome characterized by the following signs and symptoms: body aches, diarrhea, tachycardia, fever, runny nose, sneezing, piloerection, sweating, yawning, nausea or vomiting, nervousness, restlessness or irritability, shivering or trembling, abdominal cramps, weakness, and increased blood pressure. In neonates, opioid withdrawal may be life threatening if not recognized and properly treated, and may include the following signs and symptoms: convulsions, excessive crying, and hyperactive reflexes [see Warnings and Precautions (5-5.3, Adverse Reactions (6)].

Administration Instructions

Instruct patients and their family members or caregivers about the following important information:

Make sure EVZIO is present whenever persons may be intentionally or accidentally exposed to an opioid to treat serious opioid overdose (i.e., opioid emergencies).
Administer EVZIO as quickly as possible if a patient is unresponsive and an opioid overdose is suspected, even when in doubt, because prolonged respiratory depression may result in damage to the central nervous system or death. EVZIO is not a substitute for emergency medical care [see Dosage and Administration (2-2.1)].
EVZIO is user actuated and may be administered through clothing [e.g., pants, jeans, etc.] if necessary.
Inject EVZIO while pressing into the anterolateral aspect of the thigh. In pediatric patients less than 1 year of age, pinch the thigh muscle while administering EVZIO.
Upon actuation, EVZIO automatically inserts the needle intramuscularly or subcutaneously, delivers the naloxone, and retracts the needle fully into its housing. The needle is not visible before, during, or after injection.
Each EVZIO can only be used one time.
If the electronic voice instruction system on EVZIO does not work properly, EVZIO will still deliver the intended dose of naloxone hydrochloride when used according to the printed instructions on its label.
The electronic voice instructions are independent of activating EVZIO and it is not necessary to wait for the voice instructions to be completed prior to moving to the next step in the injection process.
Post-injection, the black base locks in place, a red indicator appears in the viewing window and electronic visual and audible instructions signal that EVZIO has delivered the intended dose of naloxone hydrochloride.
EVZIO’s red safety guard should not be replaced under any circumstances. However, the Trainer is designed for re-use and its red safety guard can be removed and replaced.
Periodically visually inspect the naloxone solution through the viewing window. If the solution is discolored, cloudy, or contains solid particles, replace it with a new EVZIO.
Replace EVZIO before its expiration date.

---------------------------------------------------------------------------------------------------------------

Manufactured for:
kaleo, Inc.
Richmond, VA 23219

*For California Only: This product uses batteries containing Perchlorate Material – special handling may apply. See www.dtsc.ca.gov/hazardouswaste/perchlorate

This product may be covered by one or more U.S. patents or pending patent applications. See www.kaleopharma.com/pat for details.

PATIENT PACKAGE INSERT

PATIENT INFORMATION

EVZIO® (EVV-zee-oh)
(naloxone hydrochloride injection)
Auto-Injector
for Intramuscular or Subcutaneous Use

You and your caregivers should read this Patient Information leaflet before an opioid emergency happens. This information does not take the place of talking with your healthcare provider about your medical condition or your treatment.

What is the most important information I should know about EVZIO?

EVZIO is used to temporarily reverse the effects of opioid medicines. The medicine in EVZIO has no effect in people who are not taking opioid medicines. Always carry EVZIO with you in case of an opioid emergency.

Use EVZIO right away if you or your caregiver think signs or symptoms of an opioid emergency are present, even if you are not sure, because an opioid emergency can cause severe injury or death. Signs and symptoms of an opioid emergency may include:

unusual sleepiness and you are not able to awaken the person with a loud voice or rubbing firmly on the middle of their chest (sternum)
breathing problems including slow or shallow breathing in someone difficult to awaken or they look like they are not breathing
the black circle in the center of the colored part of the eye (pupil) is very small, sometimes called “pinpoint pupils” in someone difficult to awaken

Family members, caregivers, or other people who may have to use EVZIO in an opioid emergency should know where EVZIO is stored and how to give EVZIO before an opioid emergency happens.
Get emergency medical help right away after using the first dose of EVZIO. Rescue breathing or CPR (cardiopulmonary resuscitation) may be given while waiting for emergency medical help.
The signs and symptoms of an opioid emergency can return within several minutes after EVZIO is given. If this happens, give additional injections using a new EVZIO auto-injector every 2 to 3 minutes and continue to closely watch the person until emergency help is received.

What is EVZIO?

EVZIO is a prescription medicine used in adults and children for the treatment of an opioid emergency such as an overdose or a possible opioid overdose with signs of breathing problems and severe sleepiness or not being able to respond.
EVZIO is to be given right away by a caregiver and does not take the place of emergency medical care. Get emergency medical help right away after the first dose of EVZIO, even if the person wakes up.
EVZIO is safe and effective in children for known or suspected opioid overdose.

Who should not use EVZIO?

Do not use EVZIO if you are allergic to naloxone hydrochloride or any of the ingredients in EVZIO. See the end of this leaflet for a complete list of ingredients in EVZIO.

What should I tell my healthcare provider before using EVZIO?

Before using EVZIO, tell your healthcare provider about all of your medical conditions, including if you:

have heart problems
are pregnant or plan to become pregnant. Use of EVZIO may cause withdrawal symptoms in your unborn baby. Your unborn baby should be examined by a healthcare provider right away after you use EVZIO.

Tell your healthcare provider about the medicines you take, including prescription and over-the-counter medicines, vitamins, and herbal supplements.

How should I use EVZIO?

Read the “Instructions for Use” at the end of this Patient Information leaflet for detailed information about the right way to use EVZIO.

You should use EVZIO exactly as prescribed by your healthcare provider.
Each EVZIO auto-injector contains only 1 dose of medicine.
EVZIO should be injected into the muscle or skin of the outer thigh. It can be injected through clothing if needed.
Caregivers should pinch the thigh muscle while injecting EVZIO into a child under the age of one.
A Trainer for EVZIO with a separate “Trainer Instructions for Use” leaflet is included with EVZIO. For additional training information and video instructions go to www.EVZIO.com or call 1-855-773-8946.

Practice with the Trainer for EVZIO before an opioid emergency happens to make sure you are able to safely use the real EVZIO in an emergency.
The Trainer for EVZIO does not contain a needle or medicine. It can be reused to practice your injection.
The red safety guard can be removed and replaced on the Trainer for EVZIO.

What are the possible side effects of EVZIO?

EVZIO may cause serious side effects, including:

Sudden opioid withdrawal symptoms. In someone who has been using opioids regularly, opioid withdrawal symptoms can happen suddenly after receiving EVZIO and may include:

body aches
fever
sweating
runny nose
sneezing
goose bumps
yawning
weakness
shivering or trembling
nervousness
restlessness or irritability
diarrhea
nausea or vomiting
stomach cramping
increased blood pressure
increased heart rate

Common side effects of EVZIO include dizziness and injection site redness.

In infants under 4 weeks old who have been receiving opioids regularly, sudden opioid withdrawal may be life-threatening if not treated the right way. Signs and symptoms include: seizures, crying more than usual and increased reflexes. These are not all of the possible side effects of EVZIO. Call your doctor for medical advice about side effects. You may report side effects to FDA at 1-800-FDA-1088.

How should I store EVZIO?

Store EVZIO at room temperature between 59°F to 77°F (15°C to 25°C).
Keep EVZIO in its outer case until ready to use.
Occasionally check EVZIO through the viewing window of the auto-injector. The solution should be clear. If the EVZIO solution is discolored, cloudy, or contains solid particles, replace it with a new EVZIO.
Your EVZIO has an expiration date. Replace it before the expiration date.

Keep EVZIO and all medicines out of the reach of children.

General information about the safe and effective use of EVZIO.

Medicines are sometimes prescribed for purposes other than those listed in a Patient Information leaflet. Do not use EVZIO for a condition for which it was not prescribed. You can ask your pharmacist or healthcare provider for information about EVZIO that is written for health professionals.

What are the ingredients in EVZIO?

Active ingredient: naloxone hydrochloride

Inactive ingredients: sodium chloride, hydrochloric acid to adjust pH, and water

EVZIO is not made with natural rubber latex.

Manufactured for kaleo, Inc., Richmond, VA, 23219
For more information, go to www.EVZIO.com or call 1-855-773-8946

This Patient Information has been approved by the U.S. Food and Drug Administration.Revised: 10/2016

INSTRUCTIONS FOR USE

EVZIO® (EVV-zee-oh)
(naloxone hydrochloride injection)
Auto-Injector

Read the Instructions for Use that comes with EVZIO before using it. Talk to your healthcare provider if you or your caregivers have any questions about the use of EVZIO.

Automated voice instructions

EVZIO has a speaker that provides voice instructions to help guide you through each step of the injection. See Figure A. If the voice instructions do not work for any reason, EVZIO will still work. If this happens, use EVZIO as instructed below and follow the written instructions on the EVZIO auto-injector label.

How to use EVZIO

How to know that EVZIO has been used. See Figure E.

The Black base will lock into place.
The voice instruction system will state that EVZIO has been used and the LED will blink red.
The Red safety guard cannot be replaced.
The viewing window will no longer be clear. You will see a red indicator.

What to do after EVZIO has been used:

Get emergency medical help right away.
Put the used EVZIO back into its outer case.
Do not throw away the EVZIO in household trash. Do not recycle EVZIO.
Used EVZIO should be taken to a healthcare setting for proper disposal in a sharps container.

There may be local or state laws about how to throw away used auto-injectors.*

*For California Only: This product uses batteries containing Perchlorate Material – special handling may apply. See www.dtsc.ca.gov/hazardouswaste/perchlorate

How should I store EVZIO?

Store EVZIO at room temperature between 59°F to 77°F (15°C to 25°C).
Keep EVZIO in its outer case until ready to use.
Occasionally check EVZIO through the viewing window of the auto-injector. The solution should be clear. If the EVZIO solution is discolored, cloudy, or contains solid particles, replace it with a new EVZIO.
Your EVZIO has an expiration date. Replace it before the expiration date.

Keep EVZIO and all medicines out of the reach of children.

This Instructions for Use has been approved by the U.S. Food and Drug Administration.

Manufactured for: kaleo, Inc., Richmond, VA 23219

Revised: 10/2016

INSTRUCTIONS FOR USE -TRAINER

Trainer for EVZIO®
Trainer Instructions for Use

Important:

The Trainer for EVZIO Does Not contain a needle or medicine. Always carry your real EVZIO with you in case of an opioid emergency.

Tell your family, friends, co-workers or other individuals who may need to use EVZIO during an opioid emergency, where you keep your EVZIO.

Important Information about the Trainer for EVZIO:

Inside your Trainer for EVZIO are:

batteries
a speaker that will make a beeping sound and that produces electronic voice instructions
red and green blinking lights

The Trainer for EVZIO batteries are made to last for over 1,000 demonstrations or practices.

If the electronic voice instructions do not work properly, the Trainer for EVZIO can still be used for demonstration or practice. If this happens, use the instructions below and follow the written instructions on the Trainer for EVZIO label.

What is the Trainer for EVZIO?

The Trainer for EVZIO does not contain a needle or medicine and can be reused to practice your injection.
Practice with the Trainer for EVZIO before an opioid emergency happens to make sure you are able to safely use the real EVZIO in an emergency.
A Trainer for EVZIO comes with each EVZIO prescription so that you and your caregiver can practice and demonstrate how to use EVZIO.

In case of an opioid overdose or possible opioid overdose emergency, use the real EVZIO and not the Trainer for EVZIO.

Who should practice using the Trainer for EVZIO?

Anyone who may need to help you with EVZIO in case of an opioid overdose or possible overdose emergency should practice using the Trainer for EVZIO.

Have them practice using the Trainer for EVZIO and review the Patient Information leaflet included in the packaging with your prescription of EVZIO.

For more information and video instructions on the use of EVZIO, go to http://www.EVZIO.com or call 1-855-77-EVZIO.

Practicing with the Trainer for EVZIO

Practice with the Trainer for EVZIO before an opioid emergency happens to make sure you are able to safely use the real EVZIO in the case of an opioid overdose or possible overdose emergency.
You and your caregivers should practice every day for the first week after you receive your Trainer for EVZIO, and then at least 1 time each week, to help you feel familiar with using EVZIO quickly and safely during an opioid overdose or possible opioid overdose emergency. Even when you are familiar with using the Trainer for EVZIO, continue to practice using it often.

How to use the Trainer for EVZIO

Even though the Trainer for EVZIO does not have a needle and contains no medicine, it works the same way as the real EVZIO.
Just like the real EVZIO, the Trainer for EVZIO contains an electronic voice instruction system to help guide you through each step of the injection. If the voice instructions do not work for any reason, you can still use the Trainer for EVZIO to practice using the instructions below and following the written instructions on the Trainer for EVZIO.
The Trainer for EVZIO has the same blinking red and green lights as the real EVZIO. These blinking lights help provide visual cues for each voice instruction and step.

How should I dispose of the Trainer for EVZIO?

The Trainer for EVZIO contains electronics and lithium coin cell batteries, and should be disposed of in the correct manner. Follow your State and local environmental regulations for disposal.

For California Only: This product uses batteries containing Perchlorate Material- special handling may apply. See www.dtsc.ca.gov/hazardouswaste/perchlorate

For more information or questions about the Trainer for EVZIO, go to www.EVZIO.com or call 1-855-773-8946.

How should I store the Trainer for EVZIO?

Store the Trainer for EVZIO at room temperature between 59°F to 77°F (15°C to 25°C).
Store the Trainer for EVZIO in its outer case.

This Instructions for Use has been approved by the U.S. Food and Drug Administration.

Manufactured for kaleo, Inc. Richmond, VA 23219

Revised: 10/2016